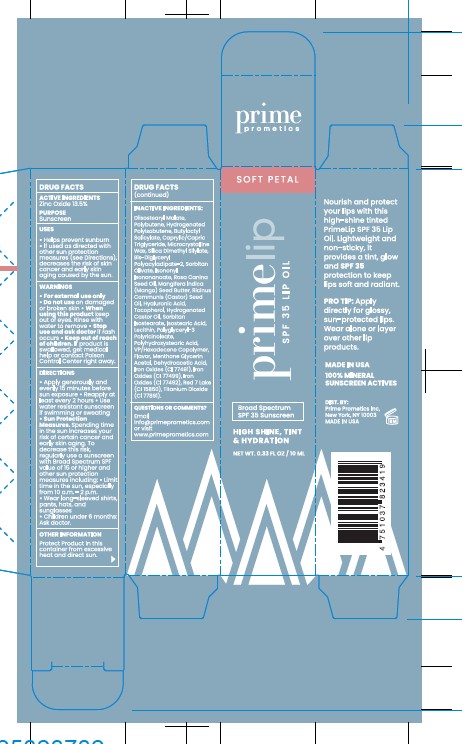 DRUG LABEL: PRIME Prometics LipOil SPF 35 Soft Petal
NDC: 68577-228 | Form: OIL
Manufacturer: COSMAX USA, CORP
Category: otc | Type: HUMAN OTC DRUG LABEL
Date: 20251231

ACTIVE INGREDIENTS: ZINC OXIDE 13.5 mg/100 mL
INACTIVE INGREDIENTS: TITANIUM DIOXIDE; DIISOSTEARYL MALATE; CI 77491; CAPRYLIC/CAPRIC TRIGLYCERIDE; ISOSTEARIC ACID; SORBITAN ISOSTEARATE; SORBITAN OLIVATE; HYDROGENATED CASTOR OIL; MICROCRYSTALLINE WAX; MANGIFERA INDICA (MANGO) SEED BUTTER; HYALURONIC ACID; BIS-DIGLYCERYL POLYACYLADIPATE-2; BUTYLOCTYL SALICYLATE; ISONONYL ISONONANOATE; VP/HEXADECENE COPOLYMER; CI 77499; SILICA DIMETHYL SILYLATE; ROSA CANINA SEED OIL; HYDROGENATED POLYISOBUTENE (450 MW); POLYGLYCERYL-3 PENTARICINOLEATE; POLYBUTENE (1400 MW); LECITHIN, SUNFLOWER; POLYHYDROXYSTEARIC ACID (2300 MW); RICINUS COMMUNIS (CASTOR) SEED OIL; DEHYDROACETIC ACID; TOCOPHEROL; MENTHONE GLYCERIN ACETAL; CI 77492; CI 19140; CI 15850

PRIME Prometics Lip Oil SPF 35 Soft Petal

Active Ingredients

Zinc Oxide 13.5%

Purpose

Sunscreen

USES

- Helps prevent sunburn
- I used as directed with other sun protection measures (see Directions), decreases the risk of skin cancer and early skin aging caused by the sun.

WARNINGS

- For external use only

- Do not useon damaged or broken skin

WHEN USING

When using this productkeep out of eyes. Rinse with water to remove

Stop use and ask doctorif rash occurs

Keep out of reach of children. If product is swallowed, get medical help or contact Poison Control Center right away.

DIRECTIONS

- Apply generously and evenly 15 minutes before sun exposure
- Reapply at least every 2 hours
- Use water resistant sunscreen if swimming or sweating
- Sun Protection Measures. Spending time in the sun increases your risk of certain cancer and early aging. To decrease this risk, regularly use a sunscreen with Broad Spectrum SPF value of 15 or higher and other sun protection measures including:
- Limit in the sun, especially from 10 a.m. - 2 p.m.
- Wear long-sleeved shirts, pants, hats, and sunglasses
- Children under 6 months:

Ask doctor.

OTHER INFORMATION

Protect Product in this container from excessive heat and direct sun

INACTIVE INGREDIENTS:

Diisostearyl Malate, Polybutene, Hydrogenated Polyisobutene, Butyloctyl Salicylate, Caprylic/Capric Triglyceride, Microcrystalline Wax, Silica Dimethyl Silylate, Bis-Diglyceryl Polyacyladipate-2, Sorbitan Olivate, Isononyl Isononanoate, Sorbitan Isostearate, Isostearic Acid, Lecithin, Polyglyceryl-3 Polyricinoleate, Polyhydroxystearic Acid, Titanium Dioxide (Cl 77891), VP/Hexadecene Copolymer, Iron Oxides (Cl 77492), Flavor, Menthone Glycerin Acetal, Red 7 Lake (Cl 15850), Iron Oxides (Cl 77491), Iron Oxides (Cl 77499), Dehydroacetic Acid, Rosa Canina Seed Oil, Mangifera Indica (Mango) Seed Butter, Ricinus Communis (Castor) Seed Oil, Hyaluronic Acid, Hydrogenated Castor Oil, and Tocopherol.